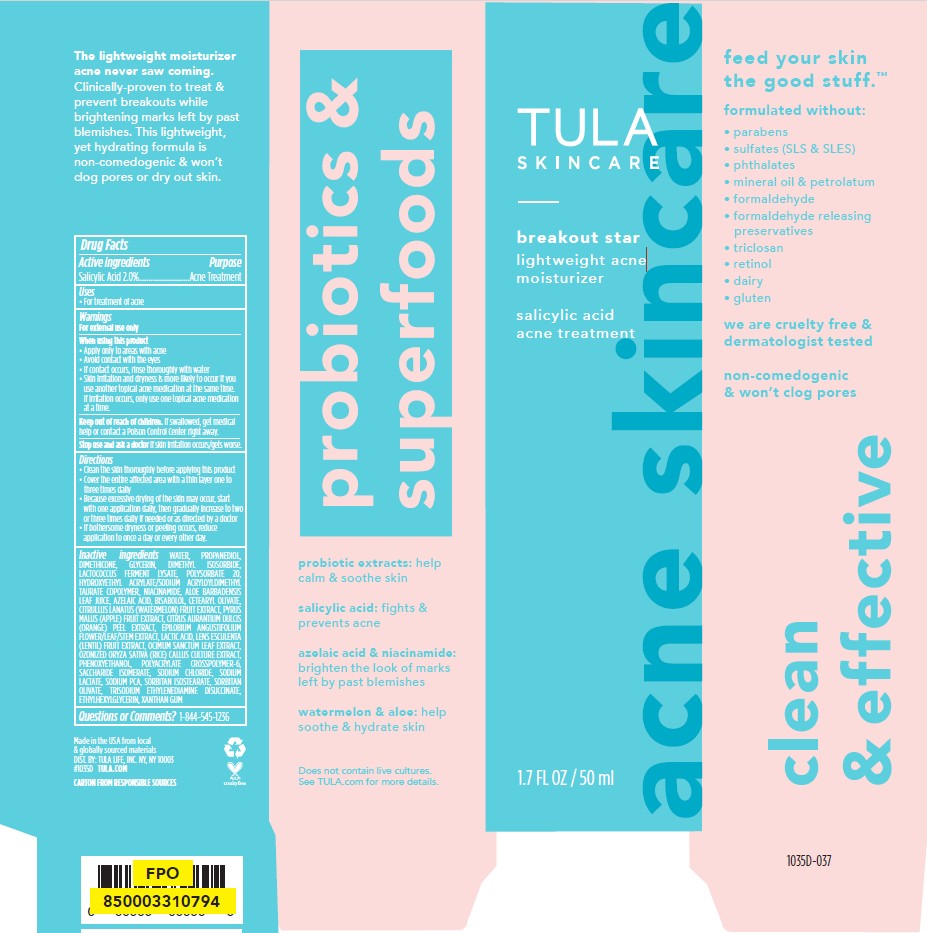 DRUG LABEL: Tula Skincare Breakout Star Lightweight Acne Moisturizer
NDC: 84126-229 | Form: CREAM
Manufacturer: The Procter & Gamble Manufacturing Company
Category: otc | Type: HUMAN OTC DRUG LABEL
Date: 20260227

ACTIVE INGREDIENTS: SALICYLIC ACID 2 g/100 mL
INACTIVE INGREDIENTS: HYDROXYETHYL ACRYLATE/SODIUM ACRYLOYLDIMETHYL TAURATE COPOLYMER (100000 MPA.S AT 1.5%); CITRUS AURANTIUM DULCIS (ORANGE) PEEL POWDER; DIMETHYL ISOSORBIDE; RICE GERM; ALOE BARBADENSIS LEAF JUICE; DIMETHICONE; WATERMELON; POLYSORBATE 20; SACCHARIDE ISOMERATE; PROPANEDIOL; PYRUS MALUS (APPLE) FRUIT; SODIUM LACTATE; HOLY BASIL LEAF; POLYACRYLATE CROSSPOLYMER-6; VICIA LENS FRUIT; SORBITAN ISOSTEARATE; SORBITAN OLIVATE; LACTIC ACID; TRISODIUM ETHYLENEDIAMINE DISUCCINATE; XANTHAN GUM; AZELAIC ACID; BISABOLOL; PHENOXYETHANOL; WATER; GLYCERIN; NIACINAMIDE; EPILOBIUM ANGUSTIFOLIUM FLOWERING TOP; ETHYLHEXYLGLYCERIN; SODIUM PCA; LACTOCOCCUS LACTIS; SODIUM CHLORIDE

Tula Skincare Breakout Star Lightweight Acne Moisturizer

Drug Facts

Active ingredients

Salicylic Acid 2%

Purpose

Acne Treatment

Uses

- For treatment of acne

WARNINGS

For external use only

When using this product

Apply only to areas with acne

Avoid contact with the eyes

If contact occurs, rinse thoroughly with water

Skin irritation and dryness is more likely to occur if you use another topical acne medication at the same time. If irritation occurs, only use one topical acne medication at a time.

Keep out of reach of children.

If swallowed, get medical help or contact a Poison Control Center right away.

Stop use and ask a doctor if skin irritation occurs/gets worse.

Directions

- Clean the skin thoroughly before applying this product
- Cover the entire affected area with a thin layer one to three times daily
- Because excessive drying of the skin may occur, start with one application daily, then gradually increase to two or three uses daily if needed or as directed by a doctor
- If bothersome dryness or peeling occurs, reduce application to once a day or every other day.

INACTIVE INGREDIENT

WATER, PROPANEDIOL, DIMETHICONE, GLYCERIN, DIMETHYL ISOSORBIDE, LACTOCOCCUS FERMENT LYSATE, POLYSORBATE 20, HYDROXYETHYL ACRYLATE/SODIUM ACRYLOYLDIMETHYL TAURATE COPOLYMER, NIACINAMIDE, ALOE BARBADENSIS LEAF JUICE, AZELAIC ACID, BISABOLOL, CETEARYL OLIVATE, CITRULLUS LANATUS (WATERMELON) FRUIT EXTRACT, PYRUS MALUS (APPLE) FRUIT EXTRACT, CITRUS AURANTIUM DULCIS (ORANGE) PEEL EXTRACT, EPILOBIUM ANGUSTIFOLIUM FLOWER/LEAF/STEM EXTRACT, LACTIC ACID, LENS ESCULENTA (LENTIL) FRUIT EXTRACT, OCIMUM SANCTUM LEAF EXTRACT, OZONIZED ORYZA SATIVA (RICE) CALLUS CULTURE EXTRACT, PHENOXYETHANOL, POLYACRYLATE CROSSPOLYMER-6, SACCHARIDE ISOMERATE, SODIUM CHLORIDE, SODIUM LACTATE, SODIUM PCA, SORBITAN ISOSTEARATE, SORBITAN OLIVATE, TRISODIUM ETHYLENEDIAMINE DISUCCINATE, ETHYLHEXYLGLYCERIN, XANTHAN GUM

Questions or Comments?:

1-844-545-1236

Made in the USA from local & globally sourced materials

DIST. BY: TULA LIFE, INC. NY, NY 10003

#1035D TULA.COM

PRINCIPAL DISPLAY PANEL - 50 mL carton

Tula Skincare

breakout star

lightweight acne

moisturizer

salicylic acid

acne treatment

50 mL (1.7 FL OZ)